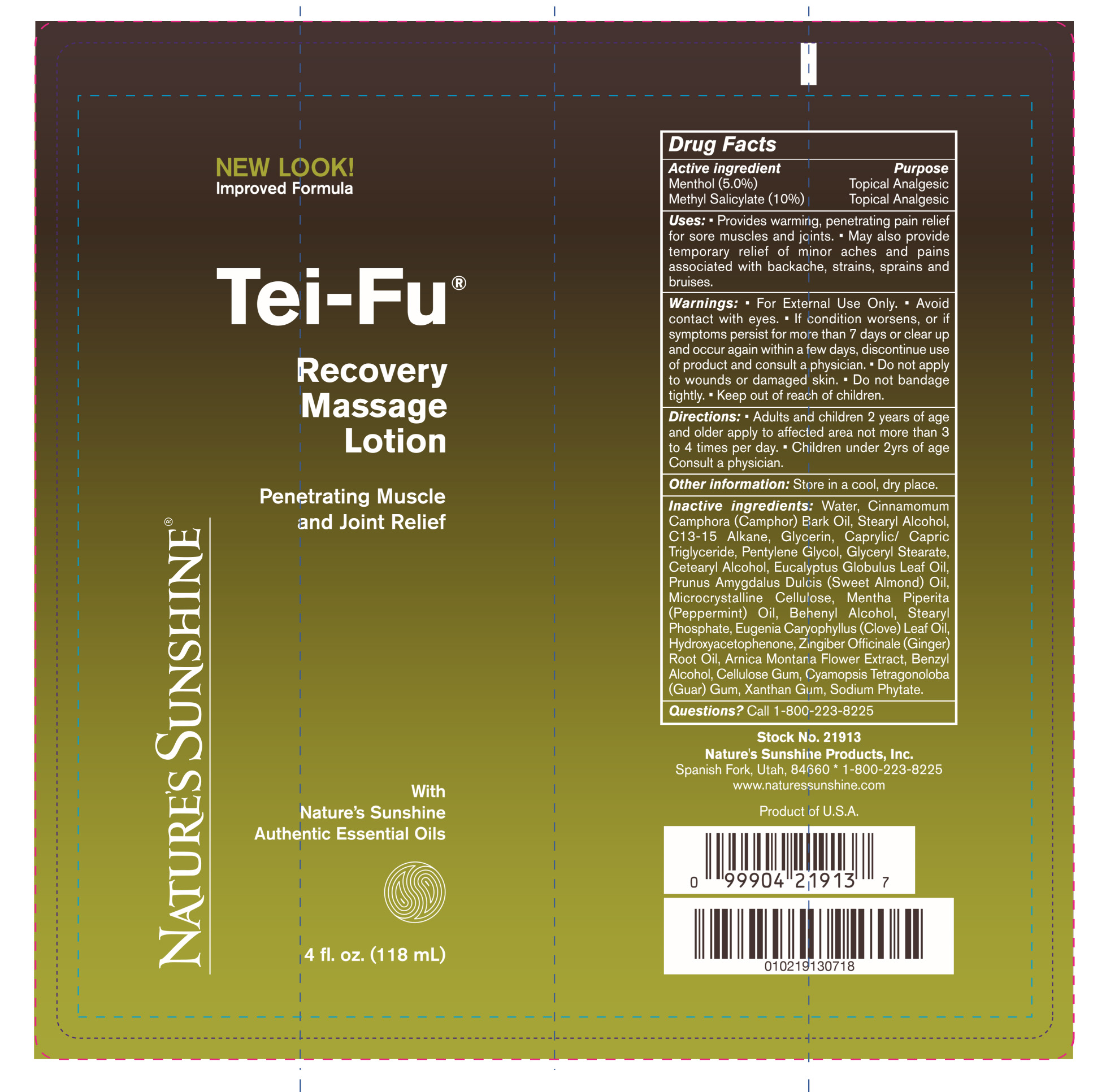 DRUG LABEL: Te-Fu Recovery Massage
NDC: 44717-539 | Form: LOTION
Manufacturer: Wasatch Product Development
Category: otc | Type: HUMAN OTC DRUG LABEL
Date: 20251010

ACTIVE INGREDIENTS: MENTHOL 5 g/100 mL; METHYL SALICYLATE 10 g/100 mL
INACTIVE INGREDIENTS: CETOSTEARYL ALCOHOL; EUCALYPTUS OIL; STEARYL PHOSPHATE; PEPPERMINT OIL; HYDROXYACETOPHENONE; ARNICA MONTANA FLOWER; CARBOXYMETHYLCELLULOSE SODIUM, UNSPECIFIED FORM; GUAR GUM; XANTHAN GUM; CAMPHOR OIL; CLOVE LEAF OIL; BENZYL ALCOHOL; PHYTATE SODIUM; C13-15 ALKANE; GLYCERIN; ALMOND OIL; GINGER OIL; STEARYL ALCOHOL; PENTYLENE GLYCOL; MEDIUM-CHAIN TRIGLYCERIDES; MICROCRYSTALLINE CELLULOSE; WATER; GLYCERYL MONOSTEARATE; DOCOSANOL

Tei-Fu recovery Massage Lotion

Active ingredient Purpose

Menthol (5.0%) Topical Analgesic

Methyl Salicylicate (10%) Topical Analgesic

Uses

Provides warming, penetrating pain relief for sore muscles and joints

May also provide temporary relief of minor aches and pains associated with backache, strains and bruises

Keep out of reach of children

INDICATIONS AND USAGE

If condition worsens, or if symptoms persist for more than 7 days or clear up and occur again within a few days, discontinue use of product and consult a physician.

Warnings

For external use only.

Avoid contact with eyes

Do not bandage tightly

Directions

Adults and children 2 year of age and older apply to affected area not more than 3 to 4 times per day

Children under 2yrs of age consult a physician.

INACTIVE INGREDIENT

Inactive ingredients: Water, Cinnamomium Camphora (Camphor) Bark Oil, Stearyl Alcohol, C13-15 Alkane, Glycerin, Caprylic/capric Triglyceride, Pentylene Glycol, Glyceryl Stearate, Cetearyl Alcohol, Eucalyptus Globulus Leaf Oil, Prunus Amygdalus Dulcis(sweet almond) Oil, Microcrystalline Cellulose, Mentha Piperita (peppermint) Oil, Behenyl Alcohol, Stearyl Phosphate, Eugenia Caryophyllus (Clove) Leaf Oil, Hydroxyacetophenone, Zingiber Officinale (ginger) Root Oil, Arnica Montana Flower Extract, Benzyl Alcohol, Cellulose Gum, Cyamopsis Tetragonoloba (Guar) Gum, Xanthan Gum, Sodium Phytate.

PACKAGE LABEL

Tei-Fu

Recovery Massage Lotion

Penetrating Muscle and Joint Relief

4fl. oz. (118 mL)